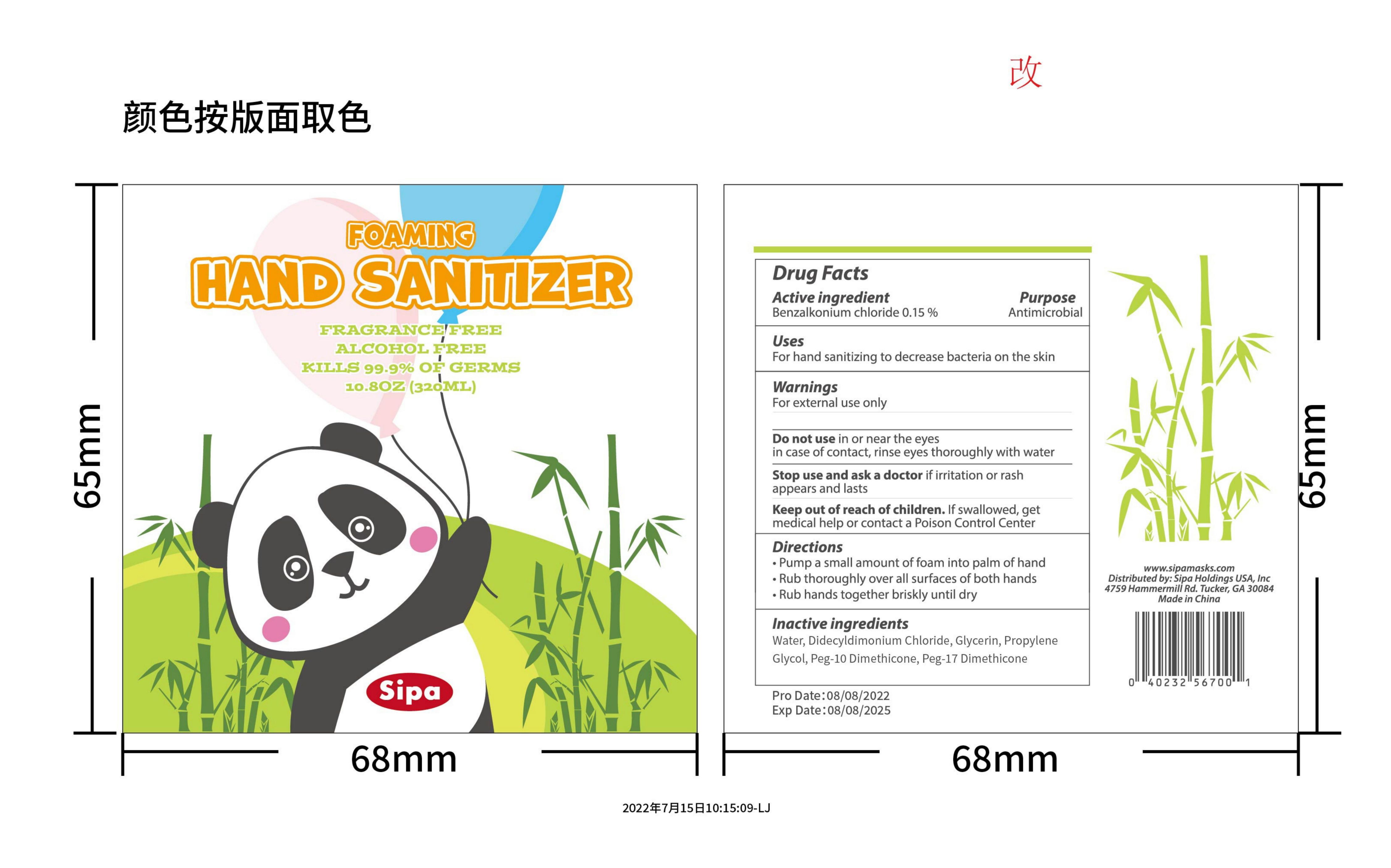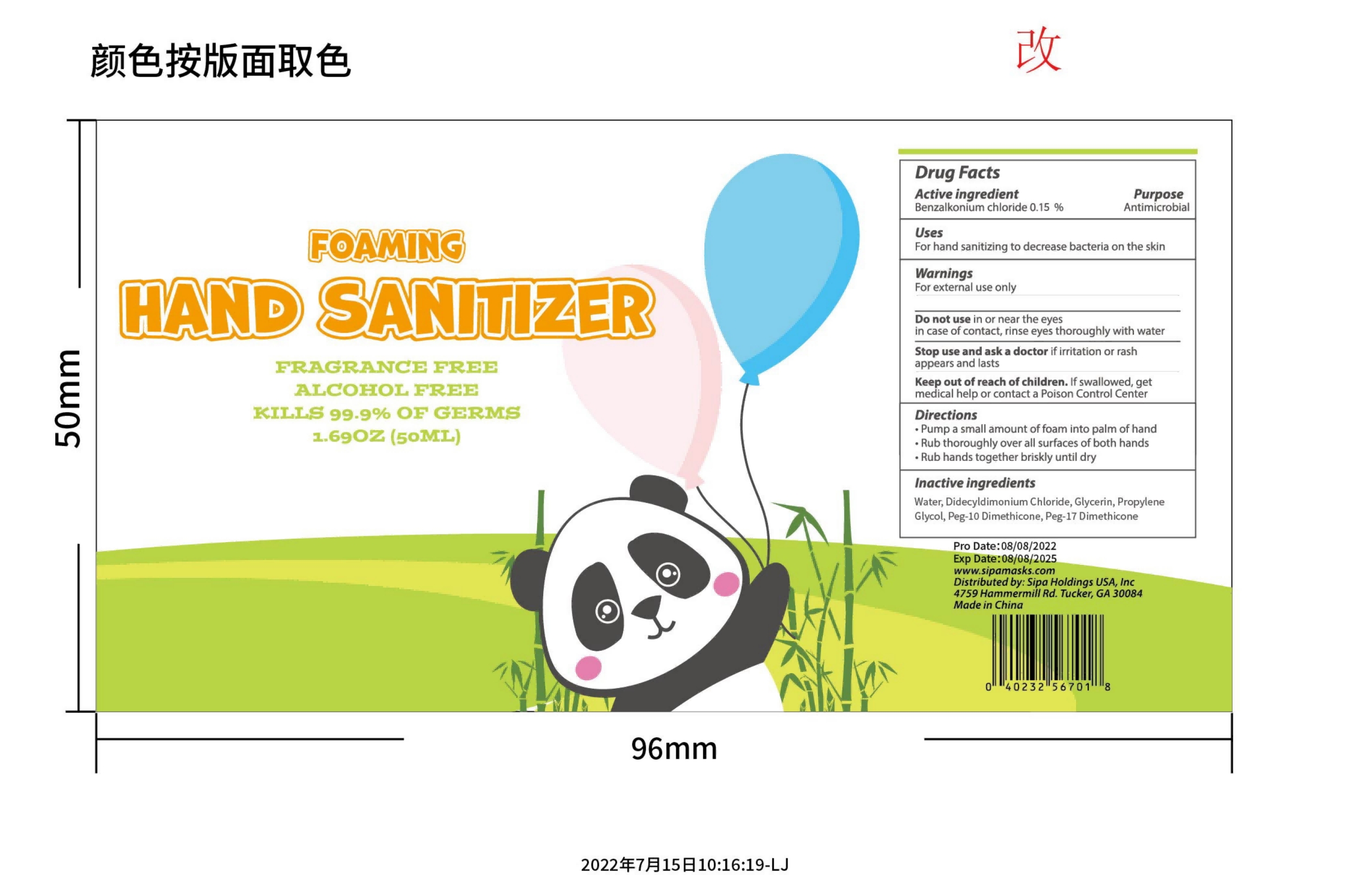 DRUG LABEL: Sipa Foam hand sanitizer with Moisturizers
NDC: 83502-001 | Form: LIQUID
Manufacturer: Tourel (Changsha)Hotel Supplies Co.,Ltd
Category: otc | Type: HUMAN OTC DRUG LABEL
Date: 20250102

ACTIVE INGREDIENTS: BENZALKONIUM CHLORIDE 0.15 g/100 mL
INACTIVE INGREDIENTS: PEG-10 DIMETHICONE (220 CST); PEG-175 DISTEARATE; DIDECYLDIMONIUM CHLORIDE; GLYCERIN; PROPYLENE GLYCOL; WATER

83502-001 Update

Active Ingredient

Benzalkonium chloride 0.15 %

Purpose

For hand sanitizing to decrease bacteria on the skin

Use

For hand sanitizing to decrease bacteria on the skin

Warnings

For external use only

Do not use

in or near the eyes in case of contact, rinse eyes thoroughly with water

When Using

Pay attention to the method of use. do not touch eyes

Stop Use

if irritation or rashappears and lasts

Ask Doctor

if irritation or rashappears and lasts

Keep Oot Of Reach Of Children

lf swallowed, getmedical help or contact a Poison Control Center right

Directions

Pump a small amount of foam into palm of handRub thoroughly over all surfaces of both handsRub hands together briskly until dry

Inactive ingredients

Water, Didecyldimonium Chloride, Glycerin, PropyleneGlycol, Peg-10 Dimethicone, Peg-17 Dimethicone